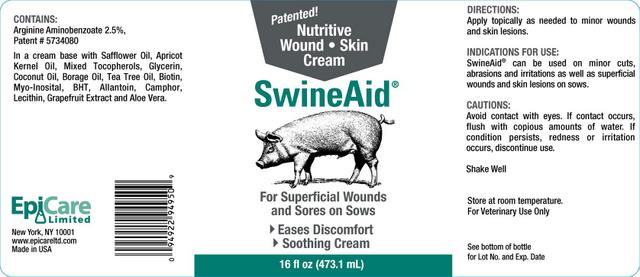 DRUG LABEL: SwineAid
NDC: 67113-004 | Form: CREAM
Manufacturer: EpiCare Limited
Category: animal | Type: OTC ANIMAL DRUG LABEL
Date: 20100908

ACTIVE INGREDIENTS: ARGININE 9.0 g/473.1 mL; AMINOBENZOIC ACID 2.8 g/473.1 mL
INACTIVE INGREDIENTS: SAFFLOWER OIL; APRICOT SEED OIL; ALPHA-TOCOPHEROL; GLYCERIN; COCONUT OIL; BORAGE OIL; TEA TREE OIL; BIOTIN; INOSITOL; BUTYLATED HYDROXYTOLUENE; ALLANTOIN; CAMPHOR OIL; LECITHIN, SOYBEAN; CITRUS PARADISI SEED; ALOE VERA LEAF

DESCRIPTION

Nutritive Wound - Skin Cream
For Superficial Wounds and Sores on Sows
- Eases Discomfort
- Soothing Cream

VETERINARY INDICATIONS

CONTAINS:

Arginine Aminobenzoate 2.5% Patent # 5734080

In a cream base with Safflower Oil, Apricot Kernal Oil, Mixed Tocopherols, Glycerin, Coconut Oil, Borage Oil, Tea Tree Oil, Biotin, Myo-Inosital, BHT, Allantoin, Camphor, Lecithin, Grapefruit Extract and Aloe Vera.

DIRECTIONS:

Apply topically as needed to minor wounds and skin lesions.

INDICATIONS FOR USE:

SwineAid can be used on minor cuts, abrasions and irritations as well as superficial wounds and skin lesions on sows.

PRECAUTIONS

CAUTIONS:

Avoid contact with eyes. If contact occurs, flush with copious amounts of water. If condition persists, redness or irritation occurs, discontinue use.

Shake Well

Store at room temperature.

For Veterinary Use Only

Principal Display Panel - 16 fl oz (473.1 mL)

Patented!

Nutritive Wound - Skin Cream

SwineAid

For Superficial Wounds and Sores on Sows

- Eases Discomfort

- Soothing Cream

16 fl oz (473.1 mL)